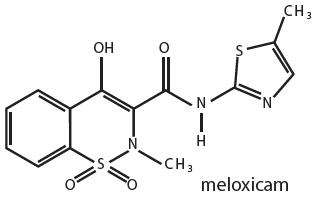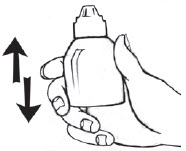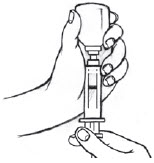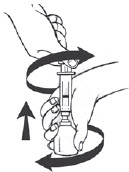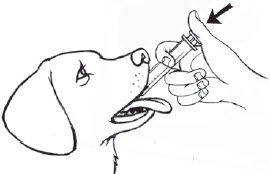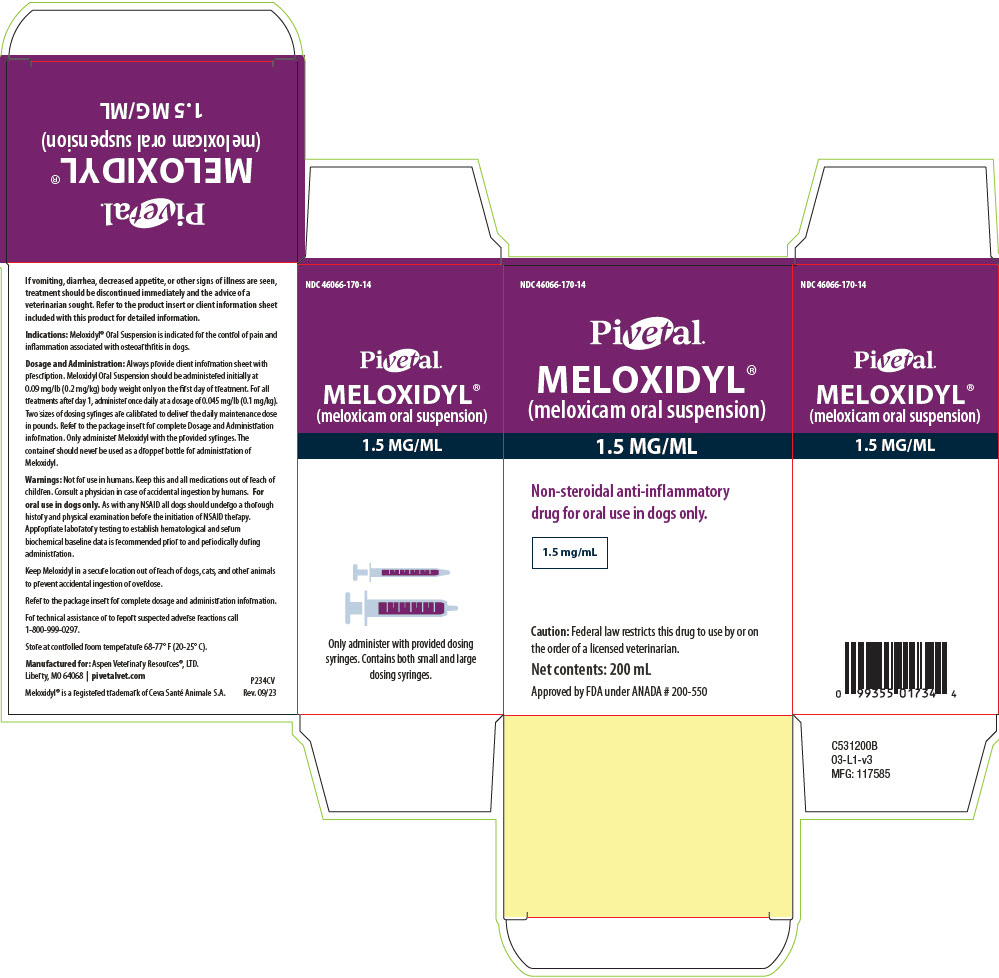 DRUG LABEL: MELOXIDYL
NDC: 46066-170 | Form: SUSPENSION
Manufacturer: Aspen Veterinary Resources, Ltd.
Category: animal | Type: PRESCRIPTION ANIMAL DRUG LABEL
Date: 20250730

ACTIVE INGREDIENTS: MELOXICAM 1.5 mg/1 mL

Meloxidyl®
(meloxicam oral suspension)
1.5 mg/mL

Professional Information Sheet

Approved by FDA under ANADA # 200-550

Meloxidyl® (meloxicam oral suspension) 1.5 mg/mL

Non-steroidal anti-inflammatory drug for oral use in dogs only

Caution: Federal law restricts this drug to use by or on the order of a licensed veterinarian.

BOXED WARNING

Warning: Repeated use of meloxicam in cats has been associated with acute renal failure and death. Do not administer additional injectable or oral meloxicam to cats. See Contraindications, Warnings, and Precautions for detailed information.

DESCRIPTION

Description: Meloxicam is a Non-Steroidal Anti-Inflammatory (NSAID) drug of the oxicam class. Each milliliter of Meloxidyl® 1.5 mg/mL Oral Suspension contains meloxicam equivalent to 1.5 milligrams and sodium benzoate (2.0 milligrams) as a preservative. The chemical name for Meloxicam is 4-Hydroxy-2-methyl-N-(5-methyl-2-thiazolyl)-2H-1,2 benzothiazine-3- carboxamide-1,1-dioxide. The formulation is a yellowish viscous suspension.

VETERINARY INDICATIONS

Indications: Meloxidyl Oral Suspension is indicated for the control of pain and inflammation associated with osteoarthritis in dogs.

Dosage and Administration: Always provide client information sheet with prescription. Carefully consider the potential benefits and risk of Meloxidyl Oral Suspension and other treatment options before deciding to use Meloxidyl Oral Suspension. Use the lowest effective dose for the shortest duration consistent with individual response. Meloxidyl Oral Suspension should be administered initially at 0.09 mg/lb (0.2 mg/kg) body weight only on the first day of treatment. For all treatments after day 1, Meloxidyl Oral Suspension should be administered once daily at a dose of 0.045 mg/lb (0.1 mg/ kg). The syringes are calibrated to deliver the daily maintenance dose in lbs.

The daily dose (0.045 mg/lb) contains 0.03 mL of Meloxidyl Oral Suspension for every 1 lb (0.45 kg) of dog body weight.

Directions for Administration:

Meloxidyl Oral Suspension is packaged with 2 sizes of dosing syringes. The small syringe (blue print) is calibrated for use in dogs under 15 lbs. The large syringe (green print) is calibrated for use in dogs 15 lbs or greater. Only administer Meloxidyl with the provided syringes. The container should never be used as a dropper bottle for administration of Meloxidyl.

Dogs under 15 lbs (6.8 kg)

Shake well before use, then remove cap. Meloxidyl Oral Suspension can be given either mixed with food or placed directly into the mouth. Particular care should be given with regard to the accuracy of dosing.

To prevent accidental overdosing of small dogs, only use the small dosing syringe. The large syringe provided cannot be used to measure doses for dogs weighing less than 15 lbs (6.8 kg). For dogs less than 15 lbs, use the small dosing syringe (blue print) provided in the package (see dosing procedure below). The small dosing syringe fits onto the bottle and has dosing marks at 0.5 lb, then in 1 lb increments (ranging from 1 to 14 lbs), designed to deliver the daily maintenance dose of 0.05 mg/lb (0.1 mg/kg).

For dogs less than 1 lb (0.45 kg), Meloxidyl can be given using the 0.5 mark on the small dosing syringe.

For dogs between 1 - 14 lbs, Meloxidyl can be given using the marks on the small dosing syringe, beginning at 1 lb and ending at 14 lbs. When using the small dosing syringe, the dog's weight should be rounded down to the nearest 1 lb increment. Replace and tighten cap after use.

Dogs 15 lbs (6.8 kg) and over

Shake well before use, then remove cap. Meloxidyl may be either mixed with food or placed directly into the mouth. Particular care should be given with regard to the accuracy of dosing.

For dogs 15 lbs or greater, use the large dosing syringe (green print) provided in the package (see dosing procedure below). The large dosing syringe fits on to the bottle and has dosing marks in 5 lb increments (ranging from 5 to 140 lbs), designed to deliver the daily maintenance dose of 0.05 mg/lb (0.1 mg/kg). When using the large syringe, the dog's weight should be rounded down to the nearest 5 lb increment. Replace and tighten cap after use.

Shake bottle well. Push down and unscrew bottle top. Attach the dosing syringe to the bottle by gently pushing the end on to the top of the bottle.

Turn the bottle/syringe upside down. Pull the plunger out until the black line on the plunger corresponds to the dog's body weight in pounds.

Turn the bottle right way up and with a twisting movement separate the dosing syringe from the bottle.

Push the plunger to empty the contents of the syringe onto food or in dog's mouth.

CONTRAINDICATIONS

Contraindications: Dogs with known hypersensitivity to meloxicam should not receive Meloxidyl Oral Suspension. Do not use Meloxidyl Oral Suspension in cats. Acute renal failure and death have been associated with the use of meloxicam in cats.

WARNINGS

Warnings: Not for use in humans. Keep this and all medications out of reach of children. Consult a physician in case of accidental ingestion by humans. For oral use in dogs only.

As with any NSAID all dogs should undergo a thorough history and physical examination before the initiation of NSAID therapy. Appropriate laboratory testing to establish hematological and serum biochemical baseline data is recommended prior to and periodically during administration. Owner should be advised to observe their dog for signs of potential drug toxicity and be given a client information sheet about Meloxidyl Oral Suspension.

Keep Meloxidyl in a secure location out of reach of dogs, cats, and other animals to prevent accidental ingestion or overdose.

PRECAUTIONS

Precautions: The safe use of Meloxidyl Oral Suspension in dogs younger than 6 months of age, dogs used for breeding, or in pregnant or lactating dogs has not been evaluated. Meloxicam Oral Suspension is not recommended for use in dogs with bleeding disorders, as safety has not been established in dogs with these disorders. As a class, cyclo-oxygenase inhibitory NSAIDs may be associated with gastrointestinal, renal and hepatic toxicity. Sensitivity to drug-associated adverse events varies with the individual patient. Dogs that have experienced adverse reactions from one NSAID may experience adverse reactions from another NSAID. Patients at greatest risk for renal toxicity are those that are dehydrated, on concomitant diuretic therapy, or those with existing renal, cardiovascular, and/or hepatic dysfunction. Concurrent administration of potentially nephrotoxic drugs should be carefully approached. NSAIDs may inhibit the prostaglandins that maintain normal homeostatic function. Such anti-prostaglandin effects may result in clinically significant disease in patients with underlying or pre-existing disease that has not been previously diagnosed. Since NSAIDs possess the potential to induce gastrointestinal ulcerations and/or perforations, concomitant use with other anti-inflammatory drugs, such as NSAIDs or corticosteroids, should be avoided. If additional pain medication is needed after administration of the total daily dose of Meloxidyl Oral Suspension, a non-NSAID or non-corticosteroid class of analgesia should be considered. The use of another NSAID is not recommended. Consider appropriate washout times when switching from corticosteroid use or from one NSAID to another in dogs. The use of concomitantly protein-bound drugs with Meloxidyl Oral Suspension has not been studied in dogs. Commonly used protein-bound drugs include cardiac, anticonvulsant and behavioral medications. The influence of concomitant drugs that may inhibit metabolism of Meloxidyl Oral Suspension has not been evaluated. Drug compatibility should be monitored in patients requiring adjunctive therapy.

ADVERSE REACTIONS

Adverse Reactions: Field safety was evaluated in 306 dogs. Based on the results of two studies, GI abnormalities (vomiting, soft stools, diarrhea, and inappetance) were the most common adverse reactions associated with the administration of meloxicam. The following table lists adverse reactions and the numbers of dogs that experienced them during the studies. Dogs may have experienced more than one episode of the adverse reaction during the study.

In foreign suspected adverse drug reaction (SADR) reporting over a 9 year period, incidences of adverse reactions related to meloxicam administration included: auto-immune hemolytic anemia (1 dog), thrombocytopenia (1 dog), polyarthritis (1 dog), nursing puppy lethargy (1 dog), and pyoderma (1 dog).

Adverse Reactions Observed During Two Field Studies
Clinical Observation | Meloxicam (n = 157) | Placebo (n = 149)
Vomiting | 40 | 23
Diarrhea/Soft Stool | 19 | 11
Bloody Stool | 1 | 0
Inappetance | 5 | 1
Bleeding Gums After Dental Procedure | 1 | 0
Lethargy/Swollen Carpus | 1 | 0
Epiphora | 1 | 0

Post-Approval Experience: (Rev 2010)

The following adverse events are based on post-approval adverse drug experience reporting. Not all adverse reactions are reported to FDA/CVM. It is not always possible to reliably estimate the adverse event frequency or establish a causal relationship to product exposure using these data. The following adverse events are listed in decreasing order of frequency by body system.

Gastrointestinal: vomiting, anorexia, diarrhea, melena, gastrointestinal ulceration

Urinary: azotemia, elevated creatinine, renal failure

Neurological/Behavioral: lethargy, depression

Hepatic: elevated liver enzymes

Dermatologic: pruritus

Death has been reported as an outcome of the adverse events listed above. Acute renal failure and death have been associated with use of meloxicam in cats.

To report suspected adverse drug events, for technical assistance or to obtain the Safety Data Sheet, contact Aspen Veterinary Resources®, LTD at 1-800-999-0297. For additional information about adverse drug experience reporting for animal drugs, contact FDA at 1-888-FDA-VETS or http://fda.gov/reportanimalae.

INFORMATION FOR OWNERS/CAREGIVERS

Information for Dog Owners: Meloxidyl, like other drugs of its class, is not free from adverse reactions. Owners should be advised of the potential for adverse reactions and be informed of the clinical signs associated with drug intolerance. Adverse reactions may include vomiting, diarrhea, decreased appetite, dark or tarry stools, increased water consumption, increased urination, pale gums due to anemia, yellowing of gums, skin or white of the eye due to jaundice, lethargy, incoordination, seizure, or behavioral changes. Serious adverse reactions associated with this drug class can occur without warning and in rare situations result in death (see Adverse Reactions). Owners should be advised to discontinue Meloxidyl Oral Suspension and contact their veterinarian immediately if signs of intolerance are observed. The vast majority of patients with drug related adverse reactions have recovered when the signs are recognized, the drug is withdrawn, and veterinary care, if appropriate, is initiated. Owners should be advised of the importance of periodic follow up for all dogs during administration of any NSAID.

CLINICAL PHARMACOLOGY

Clinical Pharmacology: Meloxicam has nearly 100% bioavailability when administered orally with food. The terminal elimination half life after a single dose is estimated to be approximately 24 hrs (+/- 30%) regardless of route of administration. There is no evidence of statistically significant gender differences in drug pharmacokinetics. Drug bioavailability, volume of distribution, and total systemic clearance remain constant up to 5 times the recommended dose for use in dogs. However, there is some evidence of enhanced drug accumulation and terminal elimination half-life prolongation when dogs are dosed for 45 days or longer.

Peak drug concentrations can be expected to occur within about 7.5 hrs after oral administration. Corresponding peak concentration is approximately 0.464 mcg/mL following a 0.2 mg/kg oral dose. The drug is 97% bound to canine plasma proteins.

SUMMARY OF SAFETY AND EFFECTIVENESS

Effectiveness: The effectiveness of meloxicam was demonstrated in two field studies involving a total of 277 dogs representing various breeds, between six months and sixteen years of age, all diagnosed with osteoarthritis. Both of the placebo-controlled, masked studies were conducted for 14 days. All dogs received 0.2 mg/kg on day 1. All dogs were maintained on 0.1 mg/kg oral meloxicam from days 2 through 14 of both studies. Parameters evaluated by veterinarians included lameness, weight-bearing, pain on palpation, and overall improvement. Parameters assessed by owners included mobility, ability to rise, limping, and overall improvement. In the first field study (n = 109), dogs showed clinical improvement with statistical significance after 14 days of meloxicam treatment for all parameters. In the second field study (n = 48), dogs receiving meloxicam showed a clinical improvement after 14 days of therapy for all parameters; however, statistical significance was demonstrated only for the overall investigator evaluation on day 7, and for the owner evaluation on day 14.

Safety:

Six Week Study

In a six week target animal safety study, meloxicam was administered orally at 1, 3, and 5X the recommended dose with no significant clinical adverse reactions. Animals in all dose groups (control, 1, 3 and 5X the recommended dose) exhibited some gastrointestinal distress (diarrhea and vomiting). No treatment-related changes were observed in hematological, blood chemistry, urinalysis, clotting time, or buccal mucosal bleeding times. Necropsy results included stomach mucosal petechiae in one control dog, two dogs at the 3X and one dog at the 5X dose. Other macroscopic changes included areas of congestion or depression of the mucosa of the jejunum or ileum in three dogs at the 1X dose and in two dogs at the 5X dose. Similar changes were also seen in two dogs in the control group. There were no macroscopic small intestinal lesions observed in dogs receiving the 3X dose. Renal enlargement was reported during the necropsy of two dogs receiving the 3X dose and two receiving the 5X dose.

Microscopic examination of the kidneys revealed minimal degeneration or slight necrosis at the tip of the papilla in three dogs at the 5X dose. Microscopic examination of the stomach showed inflammatory mucosal lesions, epithelial regenerative hyperplasia or atrophy, and sub-mucosal gland inflammation in two dogs at the recommended dose, three dogs at the 3X and four dogs at the 5X dose. Small intestinal microscopic changes included minimal focal mucosal erosion affecting the villi, and were sometimes associated with mucosal congestion. These lesions were observed in the ileum of one control dog and in the jejunum of one dog at the recommended dose and two dogs at the 5X dose.

Six Month Study

In a six month target animal safety study, meloxicam was administered orally at 1, 3, and 5X the recommended dose with no significant clinical adverse reactions. All animals in all dose groups (controls, 1, 3, and 5X the recommended dose) exhibited some gastrointestinal distress (diarrhea and vomiting). Treatment related changes seen in hematology and chemistry included decreased red blood cell counts in seven of 24 dogs (four 3X and three 5X dogs), decreased hematocrit in 18 of 24 dogs (including three control dogs), dose-related neutrophilia in one 1X, two 3X and three 5X dogs, evidence of regenerative anemia in two 3X and one 5X dog. Also noted were increased BUN in two 5X dogs and decreased albumin in one 5X dog.

Endoscopic changes consisted of reddening of the gastric mucosal surface covering less than 25% of the surface area. This was seen in three dogs at the recommended dose, three dogs at the 3X dose and two dogs at the 5X dose. Two control dogs exhibited reddening in conjunction with ulceration of the mucosa covering less than 25% of the surface area.

Gross gastrointestinal necropsy results observed included mild discoloration of the stomach or duodenum in one dog at the 3X and in one dog at the 5X dose. Multifocal pinpoint red foci were observed in the gastric fundic mucosa in one dog at the recommended dose, and in one dog at the 5X dose.

No macroscopic or microscopic renal changes were observed in any dogs receiving meloxicam in this six month study. Microscopic gastrointestinal findings were limited to one dog at the recommended dose, and two dogs at the 3X dose. Mild inflammatory mucosal infiltrate was observed in the duodenum of one dog at the recommended dose. Mild congestion of the fundic mucosa and mild myositis of the outer mural musculature of the stomach were observed in two dogs receiving the 3X dose.

HOW SUPPLIED

How Supplied: Meloxidyl® 1.5 mg/mL Oral Suspension: 10, 32, 100 and 200 mL bottles with small and large dosing syringes.

STORAGE AND HANDLING

Storage: Store at controlled room temperature 68-77° F (20-25° C).

Excursions permitted between 59° F and 86° F (15° C and 30° C). Brief exposure to temperature up to 104° F (40° C) may be tolerated provided the mean kinetic temperature does not exceed 77° F (25° C); however such exposure should be minimized.

Manufactured for: Aspen Veterinary Resources, LTD. Liberty, MO 64068 | pivetalvet.com

Meloxidyl® is a registered trademark of Ceva Santé Animale S.A.

Prod: C531010B 08-A1-v3
Mfg: 141096
Revised 09/2023

Pivetal®

Client Information Sheet for

Meloxidyl® (meloxicam oral suspension) 1.5 mg/mL

Non-steroidal anti-inflammatory drug for oral use in dogs only

This summary contains important information about Meloxidyl® 1.5 mg/mL Oral Suspension. You should read this information before you start giving your dog Meloxidyl and review it each time the prescription is refilled. This sheet is provided only as a summary and does not take the place of instructions from your veterinarian. Talk to your veterinarian if you do not understand any of this information or if you want to know more about Meloxidyl.

What is Meloxidyl®?

Meloxidyl is a prescription non-steroidal anti-inflammatory drug (NSAID) that is used to control pain and inflammation (soreness) due to osteoarthritis in dogs. Osteoarthritis (OA) is a painful condition caused by "wear and tear" of cartilage and other parts of the joints that may result in the following changes or signs in your dog: Limping or lameness, decreased activity or exercise (reluctance to stand, climb stairs, jump or run, or difficulty in performing these activities) stiffness or decreased movement of joints. Meloxidyl is given to dogs by mouth. Do not use Meloxidyl Oral Suspension in cats. Acute renal failure and death have been associated with the use of meloxicam in cats.

What Kind Of Results Can I Expect When My Dog Is On Meloxidyl® For OA?

While Meloxidyl is not a cure for osteoarthritis, it can control pain and inflammation associated with OA and improve your dog's mobility.

- Response varies from dog to dog but can be quite dramatic.
- In most dogs, improvement can be seen in a matter of days.
- If Meloxidyl is discontinued or not given as directed, your dog's pain and inflammation may come back.

What Dogs Should Not Take Meloxidyl®?

Your dog should not be given Meloxidyl if he/she:

- Has had an allergic reaction to meloxicam, the active ingredient of Meloxidyl.
- Has had an allergic reaction (such as hives, facial swelling, or red or itchy skin) to aspirin or other NSAIDs.
- Is presently taking aspirin, other NSAIDs, or corticosteroids (unless directed by your veterinarian).

Meloxidyl® Should Only Be Given To Dogs

People should not take Meloxidyl. Keep Meloxidyl and all medication out of reach of children. Call your physician immediately if you accidentally take Meloxidyl.

How To Give Meloxidyl® To Your Dog

The actual dose to be given should be prescribed by the veterinarian.

Directions for Administration:

Meloxidyl Oral Suspension is packaged with 2 sizes of dosing syringes. The small syringe (blue print) is calibrated for use in dogs under 15 lbs. The large syringe (green print) is calibrated for use in dogs 15 lbs or greater. Only administer Meloxidyl with the provided syringes. The container should never be used as a dropper bottle for administration of Meloxidyl.

Dogs under 15 lbs (6.8 kg)

Shake well before use, then remove cap. Meloxidyl Oral Suspension can be given either mixed with food or placed directly into the mouth. Particular care should be given with regard to the accuracy of dosing. To prevent accidental overdosing of small dogs, only use the small dosing syringe. The large syringe provided cannot be used to measure doses for dogs weighing less than 15 lbs (6.8 kg). For dogs less than 15 lbs, use the small dosing syringe (blue print) provided in the package (see dosing procedure below). The small dosing syringe fits onto the bottle and has dosing marks at 0.5 lb, then in 1 lb increments (ranging from 1 to 14 lbs), designed to deliver the daily maintenance dose of 0.05 mg/lb (0.1 mg/kg).

For dogs less than 1 lb (0.45 kg), Meloxidyl can be given using the 0.5 mark on the small dosing syringe.

For dogs between 1 - 14 lbs, Meloxidyl can be given using the marks on the small dosing syringe, beginning at 1 lb and ending at 14 lbs. When using the small dosing syringe, the dog's weight should be rounded down to the nearest 1 lb increment. Replace and tighten cap after use.

Dogs 15 lbs (6.8 kg) and over

Shake well before use, then remove cap. Meloxidyl may be either mixed with food or placed directly into the mouth. Particular care should be given with regard to the accuracy of dosing.

For dogs 15 lbs or greater, use the large dosing syringe (green print) provided in the package (see dosing procedure below). The large dosing syringe fits on to the bottle and has dosing marks in 5 lb increments (ranging from 5 to 140 lbs), designed to deliver the daily maintenance dose of 0.05 mg/lb (0.1 mg/kg). When using the large syringe, the dog's weight should be rounded down to the nearest 5 lb increment. Replace and tighten cap after use.

Shake bottle well. Push down and unscrew bottle top. Attach the dosing syringe to the bottle by gently pushing the end on to the top of the bottle.

Turn the bottle/syringe upside down. Pull the plunger out until the black line on the plunger corresponds to the dog's body weight in pounds.

Turn the bottle right way up and with a twisting movement separate the dosing syringe from the bottle.

Push the plunger to empty the contents of the syringe onto food or in dog's mouth.

What To Tell/Ask Your Veterinarian Before Giving Meloxidyl®

Talk to your veterinarian about:

- The signs of OA you have observed (for example limping, stiffness).
- The importance of weight control and exercise in the management of OA.
- What tests might be done before Meloxidyl is prescribed.
- How often your dog may need to be examined by your veterinarian.
- The risks and benefits of using Meloxidyl.

Tell your veterinarian if your dog has ever had the following medical problems:

- Experienced side effects from Meloxidyl or other NSAIDs, such as aspirin;
- Digestive upset (vomiting and/or diarrhea);
- Liver disease;
- Kidney disease.

Tell your veterinarian about:

- Any other medical problems or allergies that your dog has now or has had.
- All medicines that you are giving your dog or plan to give your dog, including those you can get without a prescription.

Tell your veterinarian if your dog is:

- Pregnant, nursing or if you plan to breed your dog.

What Are The Possible Side Effects That May Occur In My Dog During Meloxidyl® Therapy?

Meloxidyl, like other drugs, may cause some side effects. Serious but rare side effects have been reported in dogs taking NSAIDs. Serious side effects can occur with or without warning and in rare situations result in death.

The most common NSAID-related side effects generally involve stomach and liver or kidney problems. Look for the following side effects that can indicate your dog may be having a problem with Meloxidyl or may have another medical problem:

- Decrease or increase in appetite;
- Vomiting;
- Change in bowel movement (such as diarrhea, or black, tarry or bloody stools);
- Change in behavior (such as decreased or increased activity level, incoordination, seizure or aggression);
- Yellowing of gums, skin, or whites of the eyes (jaundice);
- Change in drinking habits (frequency, amount consumed);
- Change in urination habits (frequency, color, or smell);
- Change in skin (redness, scabs, or scratching).

It is important to stop therapy and contact your veterinarian immediately if you think your dog has a medical problem or side effect from Meloxidyl. If you have additional questions about possible side effects, talk to your veterinarian.

Can Meloxidyl® Be Given With Other Medicines?

Meloxidyl should not be given with other NSAIDs (for example aspirin, carprofen, etodolac, deracoxib) or steroids (for example, cortisone, prednisone, dexamethasone, triamcinolone).

Tell your veterinarian about all medicines you have given your dog in the past, and any medicines that you are planning to give with Meloxidyl. This should include other medicines that you can get without a prescription. Your veterinarian may want to check that all of your dog's medicines can be given together.

What Can I Do In Case My Dog Eats More Than The Prescribed Amount?

Contact your veterinarian immediately if your dog eats more than the prescribed amount of Meloxidyl.

What Else Should I Know About Meloxidyl®?

This sheet provides a summary of information about Meloxidyl. If you have any questions or concerns about Meloxidyl or osteoarthritis pain, talk to your veterinarian.

As with all prescribed medicines, Meloxidyl should only be given to the dog for which it was prescribed. Meloxidyl Oral Suspension is for use in dogs only. Do not give Meloxidyl to cats. It should be given to your dog only for the condition for which it was prescribed. It is important to periodically discuss your dog's response to Meloxidyl at regular checkups. Your veterinarian will best determine if your dog is responding as expected and if your dog should continue receiving Meloxidyl.

For technical assistance or to report suspected adverse reactions, call 1-800-999-0297.

Pivetal®

PRINCIPAL DISPLAY PANEL - 200 mL Bottle Carton

NDC 46066-170-14

Pivetal®

MELOXIDYL®

(meloxicam oral suspension)

1.5 MG/ML

Non-steroidal anti-inflammatory
drug for oral use in dogs only.

1.5 mg/mL

Caution: Federal law restricts this drug to use by or on
the order of a licensed veterinarian.

Net contents: 200 mL

Approved by FDA under ANADA # 200-550